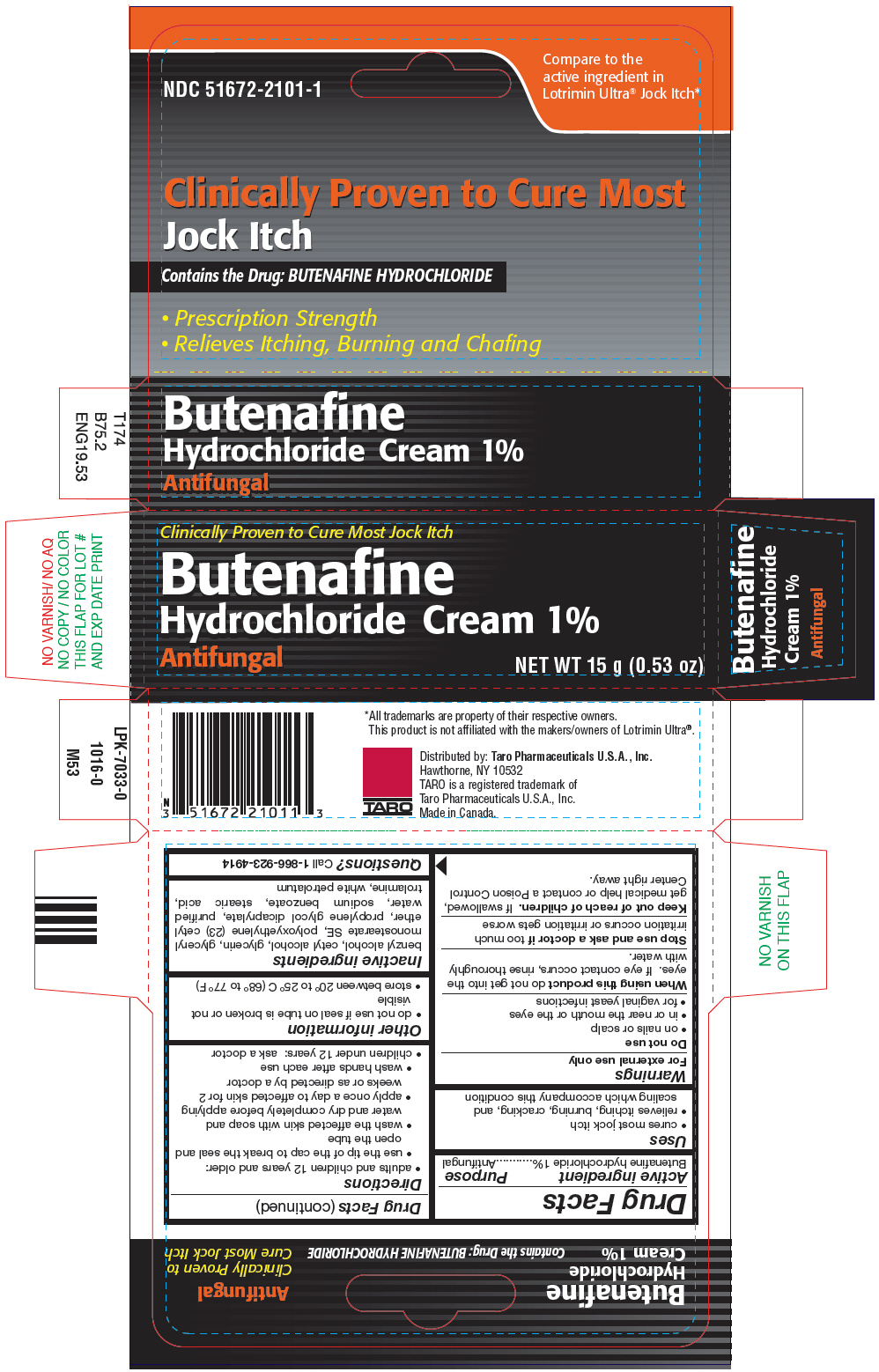 DRUG LABEL: Jock Itch
NDC: 51672-2101 | Form: CREAM
Manufacturer: Sun Pharmaceutical Industries, Inc.
Category: otc | Type: HUMAN OTC DRUG LABEL
Date: 20250703

ACTIVE INGREDIENTS: BUTENAFINE HYDROCHLORIDE 10 mg/1 g
INACTIVE INGREDIENTS: BENZYL ALCOHOL; CETYL ALCOHOL; GLYCERIN; GLYCERYL STEARATE SE; CETETH-23; PROPYLENE GLYCOL DICAPRYLATE; WATER; SODIUM BENZOATE; STEARIC ACID; TROLAMINE; PETROLATUM

Jock Itch Cream

Drug Facts

Active ingredient

Butenafine hydrochloride 1%

Purpose

Antifungal

Uses

- cures most jock itch
- relieves itching, burning, cracking, and scaling which accompany this condition

Warnings

For external use only

Do not use

- on nails or scalp
- in or near the mouth or the eyes
- for vaginal yeast infections

WHEN USING

When using this productdo not get into the eyes. If eye contact occurs, rinse thoroughly with water.

Stop use and ask a doctor iftoo much irritation occurs or irritation gets worse

Keep out of reach of children.If swallowed, get medical help or contact a Poison Control Center right away.

Directions

- adults and children 12 years and older:
  - use the tip of the cap to break the seal and open the tube
  - wash the affected skin with soap and water and dry completely before applying
  - apply once a day to affected skin for 2 weeks or as directed by a doctor
  - wash hands after each use
- children under 12 years: ask a doctor

Other information

- do not use if seal on tube is broken or not visible
- store between 20° to 25° C (68° to 77° F)

Inactive ingredients

benzyl alcohol, cetyl alcohol, glycerin, glyceryl monostearate SE, polyoxyethylene (23), propylene glycol dicaprylate, purified water, sodium benzoate, stearic acid, trolamine, white petrolatum

Questions?

Call 1-866-923-4914

Distributed by: Taro Pharmaceuticals U.S.A., Inc.
Hawthorne, NY 10532

PRINCIPAL DISPLAY PANEL - 15 g Tube Carton

Clinically Proven to Cure Most Jock Itch

Butenafine
Hydrochloride Cream 1%

Antifungal
NET WT 15 g (0.53 oz)